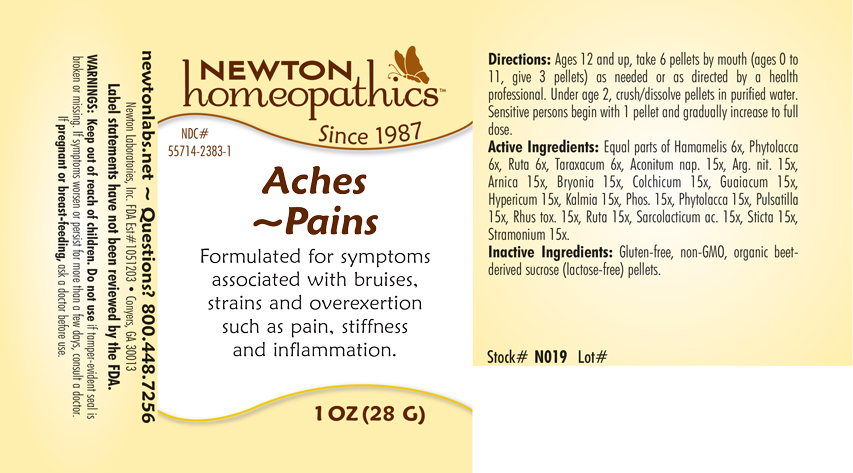 DRUG LABEL: Aches - Pains
NDC: 55714-2383 | Form: PELLET
Manufacturer: Newton Laboratories, Inc.
Category: homeopathic | Type: HUMAN OTC DRUG LABEL
Date: 20201124

ACTIVE INGREDIENTS: ACONITUM NAPELLUS 15 [hp_X]/1 g; SILVER NITRATE 15 [hp_X]/1 g; ARNICA MONTANA 15 [hp_X]/1 g; BRYONIA ALBA ROOT 15 [hp_X]/1 g; COLCHICUM AUTUMNALE BULB 15 [hp_X]/1 g; GUAIAC 15 [hp_X]/1 g; HYPERICUM PERFORATUM 15 [hp_X]/1 g; KALMIA LATIFOLIA LEAF 15 [hp_X]/1 g; PHOSPHORUS 15 [hp_X]/1 g; PHYTOLACCA AMERICANA ROOT 15 [hp_X]/1 g; PULSATILLA VULGARIS 15 [hp_X]/1 g; TOXICODENDRON PUBESCENS LEAF 15 [hp_X]/1 g; RUTA GRAVEOLENS FLOWERING TOP 15 [hp_X]/1 g; LACTIC ACID, L- 15 [hp_X]/1 g; LOBARIA PULMONARIA 15 [hp_X]/1 g; DATURA STRAMONIUM 15 [hp_X]/1 g; HAMAMELIS VIRGINIANA ROOT BARK/STEM BARK 6 [hp_X]/1 g; TARAXACUM OFFICINALE 6 [hp_X]/1 g
INACTIVE INGREDIENTS: SUCROSE

Aches - Pains 2383P

INDICATIONS & USAGE SECTION

Aches - Pains: Formulated for symptoms associated with bruises, strains and overexertion such as pain, stiffness and inflammation.

OTC - ACTIVE INGREDIENT SECTION

Active Ingredients: Equal parts of Hamamelis 6x, Phytolacca 6x, Ruta 6x, Taraxacum 6x, Aconitum nap. 15x, Arg. nit. 15x, Arnica 15x, Bryonia 15x, Colchicum 15x, Guaiacum 15x, Hypericum 15x, Kalmia 15x, Phos. 15x, Phytolacca 15x, Pulsatilla 15x, Rhus tox. 15x, Ruta 15x, Sarcolacticum ac. 15x, Sticta 15x, Stramonium 15x.

OTC - PURPOSE SECTION

Formulated for symptoms associated with bruises, strains and overexertion such as pain, stiffness and inflammation.

INACTIVE INGREDIENT SECTION

Inactive Ingredients: Gluten-free, non-GMO, organic beet-derived sucrose (lactose-free) pellets.

OTC - QUESTIONS SECTION

newtonlabs.net ~ Questions? 800-448-7256

Newton Laboratories, Inc. FDA Est # 1051203 - Conyers, GA 30013

OTC - PREGNANCY OR BREAST FEEDING SECTION

If pregnant or breast-feeding, ask a doctor before use.

OTC - KEEP OUT OF REACH OF CHILDREN SECTION

Keep out of reach of children.

DOSAGE & ADMINISTRATION SECTION

Directions: Ages 12 and up, take 6 pellets by mouth (ages 0 to 11, give 3 pellets) as needed or as directed by a health professional. Under age 2, crush/dissolve pellets in purified water. Sensitive persons begin with 1 drop and gradually increase to full dose.

WARNINGS SECTION

Warnings: Keep our of reach of children. Do not use if tamper-evident seal is broken or missing. If symptoms worsen or persist for more than a few days, consult a doctor. If pregnant or breast-feeding, ask a doctor before use.